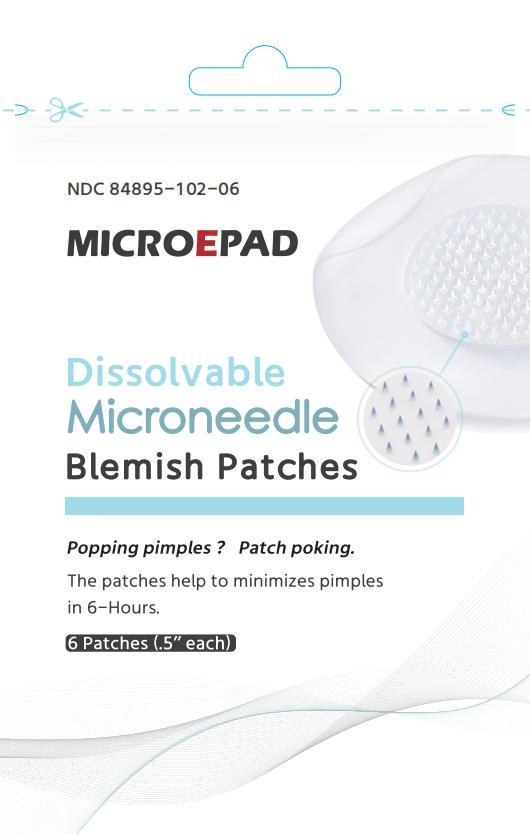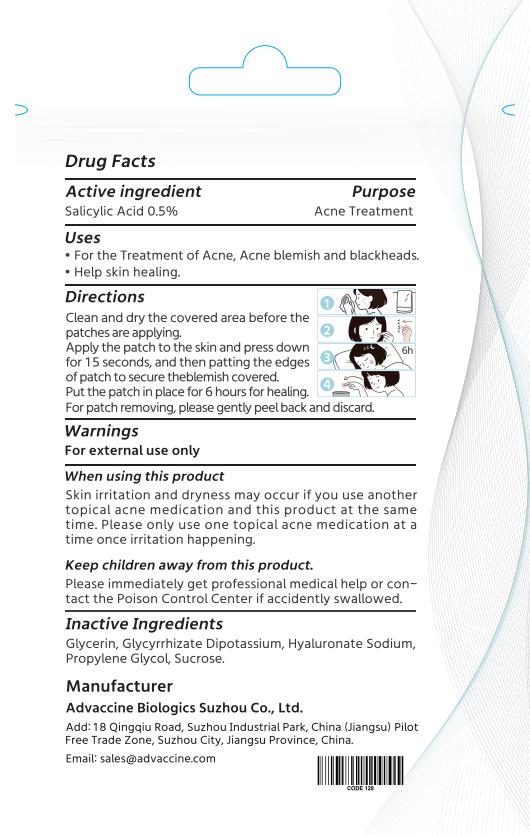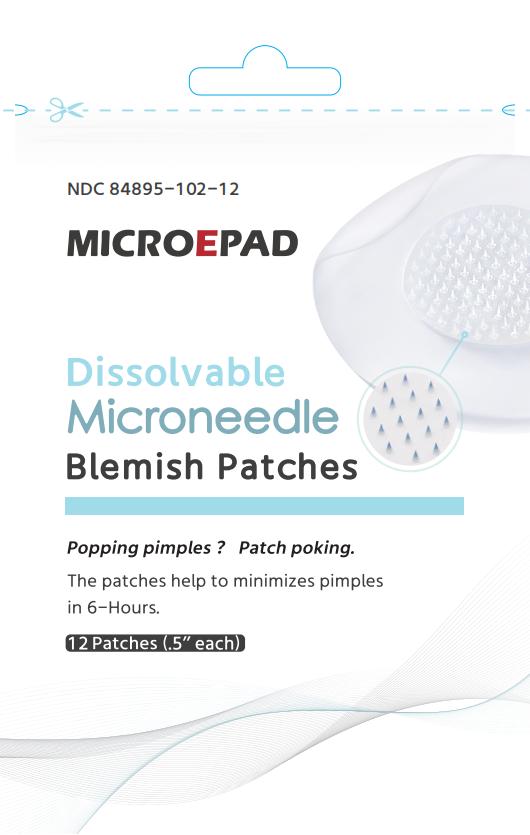 DRUG LABEL: Dissolvable Microneedle Blemish Patches
NDC: 84895-102 | Form: PATCH
Manufacturer: Advaccine Biopharmaceuticals Suzhou Co., Ltd
Category: otc | Type: HUMAN OTC DRUG LABEL
Date: 20250529

ACTIVE INGREDIENTS: SALICYLIC ACID 5 mg/1000 mg
INACTIVE INGREDIENTS: HYALURONATE SODIUM; GLYCERIN; GLYCYRRHIZINATE DIPOTASSIUM; SUCROSE; PROPYLENE GLYCOL

Active Ingredient

Salicylic Acid 0.5%

Purpose

Acne Treatment

Uses

For the treatment of acne, acne blemish and blackheads.
Help skin healing.

Directions

Clean and dry the covered area before the patches are applying.
Apply the patch to the skin and press down for 15 seconds, and then patting the edges of patch to secure the blemish covered.
Put the patch in place for 6 hours for healing.
For patch removing, please gently peel back and discard.

Warnings

For external use only

When using this product

Skin irritation and dryness may occur if you use another topical acne medication and this product at the same time. Please only use one topical acne medication at a time once irritation happening.

Keep children away from this product

Please immediately get professional medical help or contact the Poison Control Center if accidently swallowed.

Inactive Ingredient

Glycerin，Glycyrrhizate Dipotassium，Hyaluronate Sodium，Propylene Glycol，Sucrose